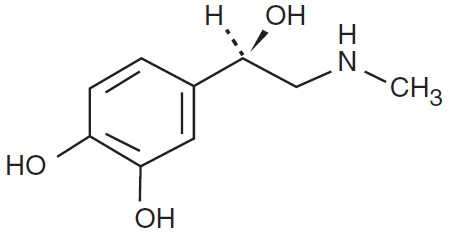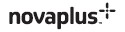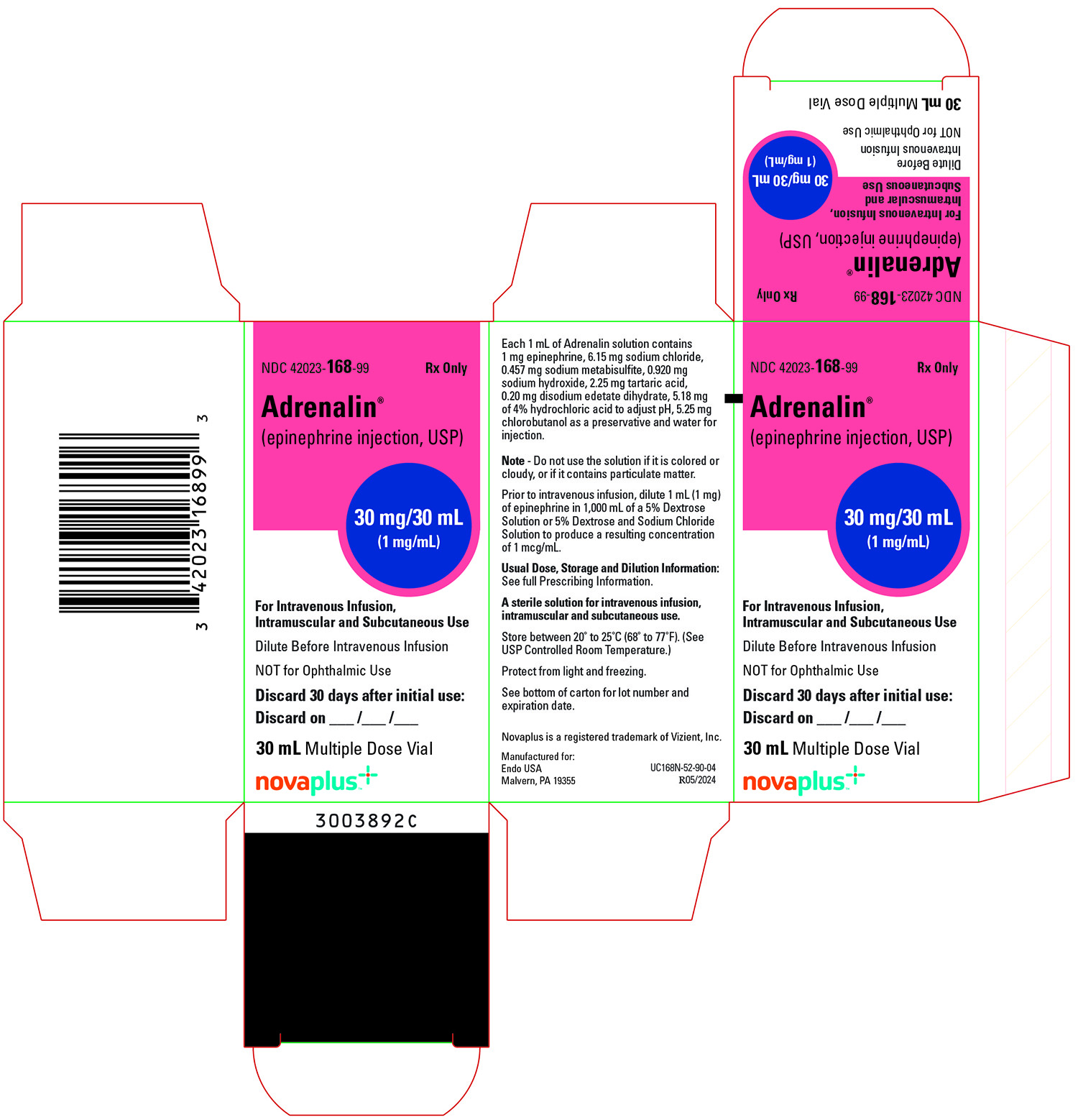 DRUG LABEL: Adrenalin
NDC: 42023-168 | Form: INJECTION
Manufacturer: Par Health USA, LLC
Category: prescription | Type: HUMAN PRESCRIPTION DRUG LABEL
Date: 20230415

ACTIVE INGREDIENTS: EPINEPHRINE 1 mg/1 mL
INACTIVE INGREDIENTS: SODIUM CHLORIDE 6.15 mg/1 mL; SODIUM METABISULFITE 0.457 mg/1 mL; SODIUM HYDROXIDE 0.920 mg/1 mL; TARTARIC ACID 2.25 mg/1 mL; EDETATE DISODIUM 0.20 mg/1 mL; CHLOROBUTANOL 5.25 mg/1 mL; HYDROCHLORIC ACID; WATER

HIGHLIGHTS OF PRESCRIBING INFORMATION

These highlights do not include all the information needed to use ADRENALIN safely and effectively. See full prescribing information for ADRENALIN.
ADRENALIN (epinephrine injection) 1 mg/mL, for
intramuscular, subcutaneous, and intravenous use
Initial U.S. Approval: 1939

1 INDICATIONS AND USAGE

Adrenalin® is a non-selective alpha and beta adrenergic agonist indicated for:

- Emergency treatment of allergic reactions (Type 1), including anaphylaxis (1.1)
- To increase mean arterial blood pressure in adult patients with hypotension associated with septic shock (1.2)

2 DOSAGE AND ADMINISTRATION

- Anaphylaxis:
  - Adults and Children 30 kg (66 lbs) or more: 0.3 mg to 0.5 mg (0.3 mL to 0.5 mL) intramuscularly or subcutaneously into anterolateral aspect of the thigh every 5 to 10 minutes as necessary (2.2)
  - Children 30 kg (66 lbs) or less: 0.01 mg/kg (0.01 mL/kg), up to 0.3 mg (0.3 mL), intramuscularly or subcutaneously into anterolateral aspect of the thigh every 5 to 10 minutes as necessary (2.2)
- Hypotension associated with septic shock:
  - Dilute epinephrine in dextrose solution prior to infusion (2.3)
  - Infuse epinephrine into a large vein (2.3)
  - Intravenous infusion rate of 0.05 mcg/kg/min to 2 mcg/kg/min, titrated to achieve desired mean arterial pressure (2.3)
  - Wean gradually (2.3)
  - See Full Prescribing Information for instructions on dilution and administration of the injection.

3 DOSAGE FORMS AND STRENGTHS

Injection: 30 mg/30 mL (1 mg/mL) multiple dose vial (3)

4 CONTRAINDICATIONS

None (4)

5 WARNINGS AND PRECAUTIONS

- Do not inject into buttocks, digits, hands, or feet (5.1)
- Avoid extravasation into tissues, which can cause local necrosis (5.3)
- May aggravate angina pectoris or produce ventricular arrhythmias (5.7)

6 ADVERSE REACTIONS

Common adverse reactions to systemically administered epinephrine include anxiety, tremor, weakness, dizziness, sweating, palpitations and pallor (6)

To report SUSPECTED ADVERSE REACTIONS, contact Endo at 1-800-828-9393 or FDA at 1-800-FDA-1088 or www.fda.gov/medwatch.

7 DRUG INTERACTIONS

- Drugs that counter the pressor effects of epinephrine include alpha blockers, vasodilators such as nitrates, diuretics, antihypertensives and ergot alkaloids. (7.1)
- Drugs that potentiate the effects of epinephrine include sympathomimetics, beta blockers, tricyclic antidepressants, MAO inhibitors, COMT inhibitors, clonidine, doxapram, oxytocin, levothyroxine sodium, quinidine and certain antihistamines. (7.2)
- Drugs that increase the arrhythmogenic potential of epinephrine include beta blockers, cyclopropane and halogenated hydrocarbon anesthetics, antihistamines, exogenous thyroid hormones, diuretics, and cardiac glycosides. Observe for development of cardiac arrhythmias. (7.3)
- Potassium-depleting drugs, including corticosteroids, diuretics, and theophylline, potentiate the hypokalemic effects of epinephrine. (7.4)

8 USE IN SPECIFIC POPULATIONS

- Elderly patients and pregnant women may be at greater risk of developing adverse reactions when epinephrine is administered parenterally (8.1, 8.5)
- Pregnancy: May cause fetal harm (8.1)

FULL PRESCRIBING INFORMATION

1 INDICATIONS AND USAGE

1.1 Anaphylaxis

Emergency treatment of allergic reactions (Type I), including anaphylaxis, which may result from insect stings or bites, foods, drugs, sera, diagnostic testing substances and other allergens, as well as idiopathic anaphylaxis or exercise-induced anaphylaxis.

1.2 Hypotension associated with Septic Shock

Adrenalin is indicated to increase mean arterial blood pressure in adult patients with hypotension associated with septic shock.

2 DOSAGE AND ADMINISTRATION

2.1 General Considerations

Inspect visually for particulate matter and discoloration prior to administration; solution should be clear and colorless. Do not use if the solution is colored or cloudy, or if it contains particulate matter.

2.2 Anaphylaxis

Inject Adrenalin intramuscularly or subcutaneously into the anterolateral aspect of the thigh, through clothing if necessary. When administering to a child, to minimize the risk of injection related injury, hold the leg firmly in place and limit movement prior to and during an injection. The injection may be repeated every 5 to 10 minutes as necessary. For intramuscular administration, use a needle long enough (at least 1/2 inch) to ensure the injection is administered into the muscle. Monitor the patient clinically for the severity of the allergic reaction and potential cardiac effects of the drug, and repeat as needed. Do not administer repeated injections at the same site, as the resulting vasoconstriction may cause tissue necrosis.

Adults and Children 30 kg (66 lbs) or more: 0.3 to 0.5 mg (0.3 to 0.5 mL) of undiluted Adrenalin administered intramuscularly or subcutaneously in the anterolateral aspect of the thigh, up to a maximum of 0.5 mg (0.5 mL) per injection, repeated every 5 to 10 minutes as necessary. Monitor clinically for reaction severity and cardiac effects.

Children less than 30 kg (66 lbs): 0.01 mg/kg (0.01 mL/kg) of undiluted Adrenalin administered intramuscularly or subcutaneously in the anterolateral aspect of the thigh, up to a maximum of 0.3 mg (0.3 mL) per injection, repeated every 5 to 10 minutes as necessary. Monitor clinically for reaction severity and cardiac effects.

2.3 Hypotension associated with Septic Shock

Dilute 1 mL (1 mg) of epinephrine from its vial to 1,000 mL of a 5 percent dextrose or 5 percent dextrose and sodium chloride solution to produce a 1 mcg per mL dilution. Administration in saline solution alone is not recommended. If indicated, administer whole blood or plasma separately.

Whenever possible, give infusions of epinephrine into a large vein. Avoid using a catheter tie-in technique, because the obstruction to blood flow around the tubing may cause stasis and increased local concentration of the drug. Avoid the veins of the leg in elderly patients or in those suffering from occlusive vascular diseases.

To provide hemodynamic support in septic shock associated hypotension in adult patients, the suggested dosing infusion rate of intravenously administered epinephrine is 0.05 to 2 mcg/kg/min, and is titrated to achieve a desired mean arterial pressure (MAP). The dosage may be adjusted periodically, such as every 10 to 15 minutes, in increments of 0.05 to 0.2 mcg/kg/min, to achieve the desired blood pressure goal.

After hemodynamic stabilization, wean incrementally over time, such as by decreasing doses of epinephrine every 10 minutes to determine if the patient can tolerate gradual withdrawal.

Adrenalin diluted in 5 percent dextrose solutions or 5 percent dextrose and sodium chloride solutions are stable for 4 hours at room temperature or 24 hours under refrigerated conditions.

3 DOSAGE FORMS AND STRENGTHS

Adrenalin injection: clear, colorless solution supplied as 30 mg/30 mL (1 mg/mL) in a multiple dose amber glass vial.

4 CONTRAINDICATIONS

None.

5 WARNINGS AND PRECAUTIONS

5.1 Incorrect Locations of Injection for Anaphylaxis

Injection into the anterolateral aspect of the thigh (vastus lateralis muscle) is the most appropriate location for administration because of its location, size, and available blood flow. Injection into (or near) smaller muscles, such as in the deltoid, is not recommended.

Do not administer repeated injections of epinephrine at the same site, as the resulting vasoconstriction may cause tissue necrosis.

Do not inject into buttock. Injection into the buttock may not provide effective treatment of anaphylaxis and has been associated with the development of Clostridial infections (gas gangrene).

Do not inject into digits, hands, or feet. Epinephrine is a strong vasoconstrictor. Accidental injection into the digits, hands or feet may result in loss of blood flow to the affected area and tissue necrosis.

5.2 Serious Infections at the Injection Site

Rare cases of serious skin and soft tissue infections, including necrotizing fasciitis and myonecrosis caused by Clostridia (gas gangrene), have been reported at the injection site following epinephrine injection for anaphylaxis. Advise patients to seek medical care if they develop signs or symptoms of infection, such as persistent redness, warmth, swelling, or tenderness, at the epinephrine injection site.

5.3 Extravasation and Tissue Necrosis with Intravenous Infusion

Avoid extravasation of epinephrine into the tissues, to prevent local necrosis. When Adrenalin is administered intravenously, check the infusion site frequently for free flow. Blanching along the course of the infused vein, sometimes without obvious extravasation, may be attributed to vasa vasorum constriction with increased permeability of the vein wall, permitting some leakage. This also may progress on rare occasions to superficial slough. Hence, if blanching occurs, consider changing the infusion site at intervals to allow the effects of local vasoconstriction to subside.

There is potential for gangrene in a lower extremity when infusions of catecholamine are given in an ankle vein.

Antidote for Extravasation Ischemia: To prevent sloughing and necrosis in areas in which extravasation has taken place, infiltrate the area with 10 mL to 15 mL of saline solution containing from 5 mg to 10 mg of phentolamine, an adrenergic blocking agent. Use a syringe with a fine hypodermic needle, with the solution being infiltrated liberally throughout the area, which is easily identified by its cold, hard, and pallid appearance. Sympathetic blockade with phentolamine causes immediate and conspicuous local hyperemic changes if the area is infiltrated within 12 hours.

5.4 Hypertension

Because individual response to epinephrine may vary significantly, monitor blood pressure frequently and titrate to avoid excessive increases in blood pressure.

Patients receiving monoamine oxidase inhibitors (MAOI) or antidepressants of the triptyline or imipramine types may experience severe, prolonged hypertension when given epinephrine.

5.5 Pulmonary Edema

Epinephrine increases cardiac output and causes peripheral vasoconstriction, which may result in pulmonary edema.

5.6 Renal Impairment

Epinephrine constricts renal blood vessels, which may result in oliguria or renal impairment.

5.7 Cardiac Arrhythmias and Ischemia

Epinephrine may induce cardiac arrhythmias and myocardial ischemia in patients, especially patients suffering from coronary artery disease, or cardiomyopathy.

5.8 Allergic Reactions Associated with Sulfite

Adrenalin contains sodium bisulfite which may cause mild to severe allergic reactions including anaphylaxis or asthmatic episodes in susceptible individuals. However, the presence of bisulfite in this product should not preclude its use for the treatment of serious allergic or other emergency situations even if the patient is sulfite-sensitive, as the alternatives to using epinephrine in a life-threatening situation may not be satisfactory.

6 ADVERSE REACTIONS

Common adverse reactions to systemically administered epinephrine include anxiety, apprehensiveness, restlessness, tremor, weakness, dizziness, sweating, palpitations, pallor, nausea and vomiting, headache, and respiratory difficulties. These symptoms occur in some persons receiving therapeutic doses of epinephrine, but are more likely to occur in patients with heart disease, hypertension, or hyperthyroidism [see Warnings and Precautions (5.7)].

The true incidence of adverse reactions associated with the systemic use of epinephrine is difficult to determine. Adverse reactions reported in observational trials, case reports, and studies are listed below by body system:

Cardiovascular: angina, arrhythmias, hypertension, pallor, palpitations, tachyarrhythmia, tachycardia, vasoconstriction, ventricular ectopy and stress cardiomyopathy.

Rapid rises in blood pressure associated with epinephrine use have produced cerebral hemorrhage, particularly in elderly patients with cardiovascular disease [see Warnings and Precautions (5.7)].

Neurological: disorientation, impaired memory, panic, psychomotor agitation, sleepiness, tingling.

Psychiatric: anxiety, apprehensiveness, restlessness.

Other:

Patients with Parkinson’s disease may experience psychomotor agitation or a temporary worsening of symptoms [see Warnings and Precautions (5.7)].

Diabetic patients may experience transient increases in blood sugar.

Injection into the buttock has resulted in cases of gas gangrene [see Warnings and Precautions (5.1)].

Rare cases of serious skin and soft tissue infections, including necrotizing fasciitis and myonecrosis caused by Clostridia (gas gangrene), have been reported following epinephrine injection in the thigh [see Warnings and Precautions (5.2)].

7 DRUG INTERACTIONS

7.1 Drugs Antagonizing Pressor Effects of Epinephrine

- α-blockers, such as phentolamine
- Vasodilators, such as nitrates
- Diuretics
- Antihypertensives
- Ergot alkaloids
- Phenothiazine antipsychotics

7.2 Drugs Potentiating Pressor Effects of Epinephrine

- Sympathomimetics
- β-blockers, such as propranolol
- Tricyclic anti-depressants
- Monoamine oxidase (MAO) inhibitors
- Catechol-O-methyl transferase (COMT) inhibitors, such as entacapone
- Clonidine
- Doxapram
- Oxytocin

7.3 Drugs Potentiating Arrhythmogenic Effects of Epinephrine

Cardiac arrhythmias are more common among patients receiving any of the following drugs [see Warnings and Precautions (5.7) and Adverse Reactions (6)].

- β-blockers, such as propranolol
- Cyclopropane or halogenated hydrocarbon anesthetics, such as halothane
- Antihistamines
- Thyroid hormones
- Diuretics
- Cardiac glycosides, such as digitalis glycosides
- Quinidine

7.4 Drugs Potentiating Hypokalemic Effects of Epinephrine

- Potassium depleting diuretics
- Corticosteroids
- Theophylline

8 USE IN SPECIFIC POPULATIONS

8.1 Pregnancy

Risk Summary

Prolonged experience with epinephrine use in pregnant women over several decades, based on published literature, do not identify a drug associated risk of major birth defects, miscarriage or adverse maternal or fetal outcomes. However, there are risks to the mother and fetus associated with epinephrine use during labor or delivery (see Clinical Considerations). In animal reproduction studies, epinephrine administered by the subcutaneous route to pregnant rabbits, mice, and hamsters, during the period of organogenesis, resulted in adverse developmental effects (including gastroschisis, and embryonic lethality, and delayed skeletal ossification) at doses approximately 2 times the maximum recommended daily intramuscular, subcutaneous, or intravenous dose (see Data).

The estimated background risk of major birth defects and miscarriage for the indicated population is unknown. All pregnancies have a background risk of birth defect, loss, or other adverse outcomes. In the United States general population, the estimated background risk of major birth defects and miscarriage in clinically recognized pregnancies is 2 to 4% and 15 to 20%, respectively.

Clinical Considerations

Disease-associated maternal and/or embryo/fetal risk

During pregnancy, anaphylaxis can be catastrophic and can lead to hypoxic-ischemic encephalopathy and permanent central nervous system damage or death in the mother and, more commonly, in the fetus or neonate. The prevalence of anaphylaxis occurring during pregnancy is reported to be approximately 3 cases per 100,000 deliveries.

Management of anaphylaxis during pregnancy is similar to management in the general population. Epinephrine is the first line-medication of choice for treatment of anaphylaxis; it should be used in the same manner in pregnant and non-pregnant patients. In conjunction with the administration of epinephrine, the patient should seek immediate medical or hospital care.

Hypotension associated with septic shock is a medical emergency in pregnancy which can be fatal if left untreated. Delaying treatment in pregnant women with hypotension associated with septic shock may increase the risk of maternal and fetal morbidity and mortality. Life-sustaining therapy for the pregnant woman should not be withheld due to potential concerns regarding the effects of epinephrine on the fetus.

Labor or Delivery

Epinephrine usually inhibits spontaneous or oxytocin induced contractions of the pregnant human uterus and may delay the second stage of labor. Avoid epinephrine during the second stage of labor. In dosage sufficient to reduce uterine contractions, the drug may cause a prolonged period of uterine atony with hemorrhage. Avoid epinephrine in obstetrics when maternal blood pressure exceeds 130/80 mmHg.

Although epinephrine may improve maternal hypotension associated with septic shock and anaphylaxis, it may result in uterine vasoconstriction, decreased uterine blood flow, and fetal anoxia.

Data

Animal Data

In an embryofetal development study with pregnant rabbits dosed during the period of organogenesis (on days 3 to 5, 6 to 7 or 7 to 9 of gestation), epinephrine caused teratogenic effects (including gastroschisis) at doses approximately 15 times the maximum recommended intramuscular, subcutaneous, or intravenous dose (on a mg/m^2 basis at a maternal subcutaneous dose of 1.2 mg/kg/day for two to three days). Animals treated on days 6 to 7 had decreased number of implantations.

In an embryofetal development study, pregnant mice were administered epinephrine (0.1 to 10 mg/kg/day) on Gestation Days 6 to 15. Teratogenic effects, embryonic lethality, and delays in skeletal ossification were observed at approximately 3 times the maximum recommended intramuscular, subcutaneous, or intravenous dose (on a mg/m^2 basis at maternal subcutaneous dose of 1 mg/kg/day for 10 days). These effects were not seen in mice at approximately 2 times the maximum recommended daily intramuscular or subcutaneous dose (on a mg/m^2 basis at a subcutaneous maternal dose of 0.5 mg/kg/day for 10 days).

In an embryofetal development study with pregnant hamsters dosed during the period of organogenesis from gestation days 7 to 10, epinephrine produced reductions in litter size and delayed skeletal ossification at doses approximately 2 times the maximum recommended intramuscular, subcutaneous, or intravenous dose (on a mg/m^2 basis at a maternal subcutaneous dose of 0.5 mg/kg/day).

8.2 Lactation

Risk Summary

There is no information regarding the presence of epinephrine in human milk or the effects of epinephrine on the breastfed infant or on milk production. However, due to its poor oral bioavailability and short half-life, epinephrine exposure is expected to be very low in the breastfed infant.

Epinephrine is the first-line medication of choice for treatment of anaphylaxis; it should be used in the same manner for anaphylaxis in breastfeeding and non-breastfeeding patients.

8.4 Pediatric Use

Clinical use data support weight-based dosing for treatment of anaphylaxis in pediatric patients, and other reported clinical experience with the use of epinephrine suggests that the adverse reactions seen in children are similar in nature and extent to those both expected and reported in adults.

Safety and effectiveness of epinephrine in pediatric patients with septic shock have not been established.

8.5 Geriatric Use

Clinical studies for the treatment of anaphylaxis have not been performed in subjects aged 65 and over to determine whether they respond differently from younger subjects. However, other reported clinical experience with use of epinephrine for the treatment of anaphylaxis has identified that geriatric patients may be particularly sensitive to the effects of epinephrine. Therefore, for the treatment of anaphylaxis, consider starting with a lower dose to take into account potential concomitant disease or other drug therapy.

Clinical studies of epinephrine for the treatment of hypotension associated with septic shock did not include sufficient numbers of subjects aged 65 and over to determine whether they respond differently from younger subjects. Other reported clinical experience has not identified differences in responses between the elderly and younger patients. In general, dose selection for an elderly patient should be cautious, usually starting at the low end of the dosing range, reflecting the greater frequency of decreased hepatic, renal, or cardiac function, and of concomitant disease or other drug therapy.

10 OVERDOSAGE

Overdosage of epinephrine may produce extremely elevated arterial pressure, which may result in cerebrovascular hemorrhage, particularly in elderly patients. Overdosage may also result in pulmonary edema because of peripheral vascular constriction together with cardiac stimulation. Epinephrine overdosage can also cause transient bradycardia followed by tachycardia and these may be accompanied by potentially fatal cardiac arrhythmias. Premature ventricular contractions may appear within one minute after injection and may be followed by multifocal ventricular tachycardia (prefibrillation rhythm). Subsidence of the ventricular effects may be followed by atrial tachycardia and occasionally by atrioventricular block. Myocardial ischemia and infarction, cardiomyopathy, extreme pallor and coldness of the skin, metabolic acidosis due to elevated blood lactic acid levels, and renal insufficiency have also been reported.

Epinephrine is rapidly inactivated in the body and treatment following overdose with epinephrine is primarily supportive. Treatment of pulmonary edema consists of a rapidly acting alpha-adrenergic blocking drug (such as phentolamine mesylate) and respiratory support. Treatment of arrhythmias consists of administration of a beta-adrenergic blocking drug (such as propranolol). If necessary, pressor effects may be counteracted by rapidly acting vasodilators or α-adrenergic blocking drugs. If prolonged hypotension follows such measures, it may be necessary to administer another pressor drug.

11 DESCRIPTION

Adrenalin (epinephrine injection, USP) is a clear, colorless, sterile solution containing 1 mg/mL epinephrine, packaged as 30 mL of solution in a multiple dose amber glass vial. In the 30 mL vial, each 1 mL of Adrenalin solution contains 1 mg epinephrine, 6.15 mg sodium chloride, 0.457 mg sodium metabisulfite, 0.920 mg sodium hydroxide, 2.25 mg tartaric acid, 0.20 mg disodium edetate dihydrate, 5.18 mg of 4% hydrochloric acid to adjust pH, 5.25 mg chlorobutanol as a preservative and water for injection. The pH range is 2.2-5.0.

Epinephrine is a sympathomimetic catecholamine. The chemical name of epinephrine is: 1,2-Benzenediol, 4-[(1R)-1-hydroxy-2-(methylamino)ethyl]-, or (-)-3,4-Dihydroxy-α-[2-(methylamino)ethyl]benzyl alcohol.

The chemical structure of epinephrine is:

The molecular weight of epinephrine is 183.2.

Epinephrine solution deteriorates rapidly on exposure to air or light, turning pink from oxidation to adrenochrome and brown from the formation of melanin.

12 CLINICAL PHARMACOLOGY

12.1 Mechanism of Action

Epinephrine acts on both alpha and beta-adrenergic receptors. The mechanism of the rise in blood pressure is 3-fold: a direct myocardial stimulation that increases the strength of ventricular contraction (positive inotropic action), an increased heart rate (positive chronotropic action), and peripheral vasoconstriction.

12.2 Pharmacodynamics

Epinephrine increases glycogenolysis, reduces glucose up take by tissues, and inhibits insulin release in the pancreas, resulting in hyperglycemia and increased blood lactic acid.

Intramuscular and subcutaneous use for anaphylaxis

Through its action on alpha-adrenergic receptors, epinephrine lessens the vasodilation and increased vascular permeability that occurs during anaphylaxis, which can lead to loss of intravascular fluid volume and hypotension.

Through its action on beta-adrenergic receptors, epinephrine causes bronchial smooth muscle relaxation and helps alleviate bronchospasm, wheezing and dyspnea that may occur during anaphylaxis.

Epinephrine also alleviates pruritus, urticaria, and angioedema and may relieve gastrointestinal and genitourinary symptoms associated with anaphylaxis because of its relaxer effects on the smooth muscle of the stomach, intestine, uterus and urinary bladder.

Intravenous use for hypotension associated with septic shock

When administered parenterally, epinephrine has a rapid onset and short duration of action.

Following intravenous administration of epinephrine, increases in systolic blood pressure and heart rate are observed. Decreases in systemic vascular resistance and diastolic blood pressure are observed at low doses of epinephrine because of β2-mediated vasodilation, but are overtaken by α1-mediated peripheral vasoconstriction at higher doses leading to increase in diastolic blood pressure. The onset of blood pressure increase following an intravenous dose of epinephrine is < 5 minutes and the time to offset blood pressure response occurs within 15 minutes. Most vascular beds are constricted including renal, splanchnic, mucosal and skin.

Epinephrine causes mydriasis when administered parenterally.

12.3 Pharmacokinetics

Following intravenous injection, epinephrine is rapidly cleared from the plasma with an effective half-life of < 5 minutes. A pharmacokinetic steady state following continuous intravenous infusion is achieved within 10 to 15 minutes. In patients with septic shock, epinephrine displays dose-proportional pharmacokinetics in the infusion dose range of 0.03 to 1.7 mcg/kg/min.

Epinephrine is extensively metabolized with only a small amount excreted unchanged.

Epinephrine is rapidly degraded to vanillylmandelic acid, an inactive metabolite, by monoamine oxidase and catechol-O-methyltransferase that are abundantly expressed in the liver, kidneys and other extraneuronal tissues. The tissues with the highest contribution to removal of circulating exogenous epinephrine are the liver (32%), kidneys (25%), skeletal muscle (20%), and mesenteric organs (12%).

Specific Populations

Elderly

In a pharmacokinetic study of 45-minute epinephrine infusions given to healthy men aged 20 to 25 years and healthy men aged 60 to 65 years, the mean plasma metabolic clearance rate of epinephrine at steady state was greater among the older men (144.8 versus 78 mL/kg/min for a 0.0143 mcg/kg/min infusion).

Body Weight

Body weight has been found to influence epinephrine pharmacokinetics. Higher body weight was associated with a higher plasma epinephrine clearance and a lower concentration plateau.

13 NONCLINICAL TOXICOLOGY

13.1 Carcinogenesis, Mutagenesis, Impairment of Fertility

Long-term studies to evaluate the carcinogenic potential of epinephrine have not been conducted.

Epinephrine and other catecholamines have been shown to have mutagenic potential in vitro. Epinephrine was positive in the Salmonella bacterial reverse mutation assay, positive in the mouse lymphoma assay, and negative in the in vivo micronucleus assay. Epinephrine is an oxidative mutagen based on the E. coli WP2 Mutoxitest bacterial reverse mutation assay. This should not prevent the use of epinephrine under the conditions noted under Indications and Usage (1).

The potential for epinephrine to impair reproductive performance has not been evaluated, but epinephrine has been shown to decrease implantation in female rabbits dosed subcutaneously with 1.2 mg/kg/day (15-fold the highest human intramuscular or subcutaneous daily dose) during gestation days 3 to 9.

16 HOW SUPPLIED/STORAGE AND HANDLING

Adrenalin 30 mg/30 mL (1 mg/mL) Multiple Dose Vials:

Each carton contains 1 multiple dose vial containing 30 mg/30 mL (1 mg/mL) Adrenalin (epinephrine injection, USP) solution in a 36 mL amber glass vial.

NDC 42023-168-99 30 mL Multiple Dose Vial

Vial and contents must be discarded 30 days after initial use.

STORAGE AND HANDLING

Store between 20° to 25°C (68° to 77°F) [See USP Controlled Room Temperature]. Epinephrine is light sensitive. Protect from light and freezing.

Inspect visually for particulate matter and discoloration prior to administration. Do not use the solution if it is colored or cloudy, or if it contains particulate matter.

17 PATIENT COUNSELING INFORMATION

Advise patients or their caregivers about common adverse reactions associated with the use of epinephrine including an increase in heart rate, the sensation of a more forceful heartbeat, palpitations, sweating, nausea and vomiting, difficulty breathing, pallor, dizziness, weakness or shakiness, headache, apprehension, nervousness, or anxiety. These symptoms and signs usually subside rapidly, especially with rest, quiet and recumbent positioning.

Warn patients with a good response to initial treatment about the possibility of recurrence of symptoms and instruct patients to obtain proper medical attention if symptoms return.

Warn patients with diabetes that they may develop increased blood glucose levels following epinephrine administration.

Rare cases of serious skin and soft tissue infections, including necrotizing fasciitis and myonecrosis caused by Clostridia (gas gangrene), have been reported at the injection site following epinephrine injection for anaphylaxis. Advise patients to seek medical care if they develop signs or symptoms of infection, such as persistent redness, warmth, swelling, or tenderness, at the epinephrine injection site [see Warnings and Precautions (5.2)].

Manufactured for:

Endo USA

Malvern, PA 19355

© 2024 Endo, Inc. or one of its affiliates.

Novaplus is a registered trademark of Vizient, Inc.

R05/2024